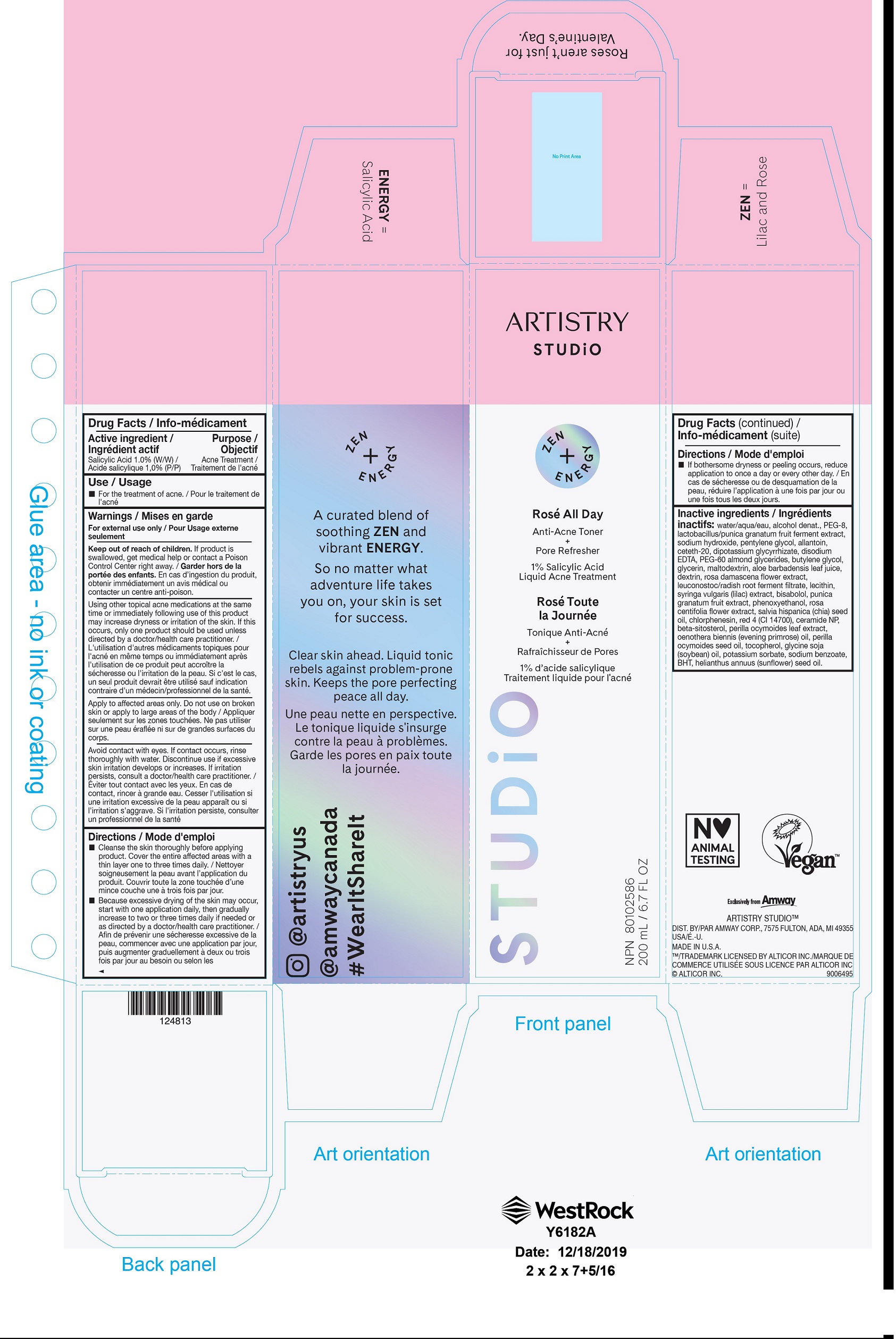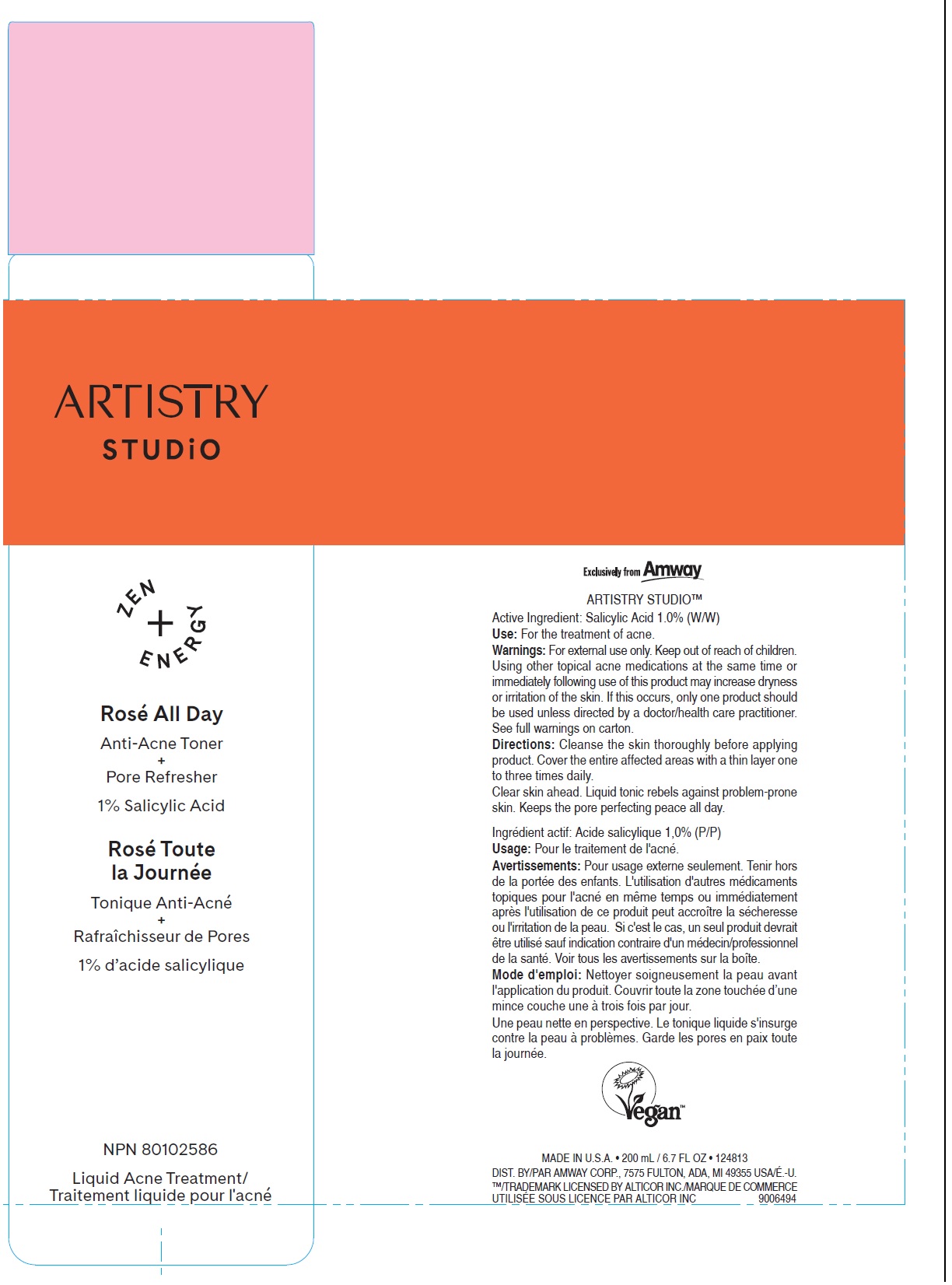 DRUG LABEL: ARTISTRY STUDiO Rose All Day Anti Acne Toner Pore Refresher
NDC: 10056-410 | Form: LIQUID
Manufacturer: Access Business Group LLC
Category: otc | Type: HUMAN OTC DRUG LABEL
Date: 20231021

ACTIVE INGREDIENTS: SALICYLIC ACID 10 mg/1 mL
INACTIVE INGREDIENTS: WATER; ALCOHOL; POLYETHYLENE GLYCOL 400; SODIUM HYDROXIDE; PENTYLENE GLYCOL; ALLANTOIN; CETETH-20; GLYCYRRHIZINATE DIPOTASSIUM; EDETATE DISODIUM ANHYDROUS; PEG-60 ALMOND GLYCERIDES; BUTYLENE GLYCOL; GLYCERIN; MALTODEXTRIN; ALOE VERA LEAF; ICODEXTRIN; ROSA X DAMASCENA FLOWER; LEUCONOSTOC/RADISH ROOT FERMENT FILTRATE; EGG PHOSPHOLIPIDS; SYRINGA VULGARIS WHOLE; LEVOMENOL; POMEGRANATE; PHENOXYETHANOL; ROSA CENTIFOLIA FLOWER; CHIA SEED OIL; CHLORPHENESIN; FD&C RED NO. 4; CERAMIDE NP; .BETA.-SITOSTEROL; PERILLA FRUTESCENS LEAF; EVENING PRIMROSE OIL; PERILLA FRUTESCENS SEED OIL; TOCOPHEROL; SOYBEAN OIL; POTASSIUM SORBATE; SODIUM BENZOATE; BUTYLATED HYDROXYTOLUENE; SUNFLOWER OIL

ARTISTRY STUDiO Rose All Day - Anti-Acne Toner + Pore Refresher

Active ingredient

Salicylic Acid 1.0% (W/W)

Purpose

Acne Treatment

Use

- For the treatment of acne.

Warnings

For external use only

Keep out of reach of children.

If product is swallowed, get medical help or contact a Poison Control Center right away.

Using other topical acne medications at the same time or immediately following use of this product may increase dryness or irritation of the skin. If this occurs, only one product should be used unless directed by a doctor/health care practitioner.

Apply to affected areas only

Do not use

on broken skin or apply to large areas of the body

Avoid contact with eyes. If contact occurs, rinse thoroughly with water. Discontinue use if excessive skin irritation develops or increases. If irritation persists, consult a doctor/health care practitioner.

Directions

- Cleanse the skin thoroughly before applying product. Cover the entire affected areas with a thin layer one to three times daily.
- Because excessive drying of the skin may occur, start with one application daily, then gradually increase to two or three times daily if needed or as directed by a doctor/health care practitioner.
- If bothersome dryness or peeling occurs, reduce application to once a day or every other day.

Inactive ingredients

water/aqua, alcohol denat., PEG-8, lactobacillus/punica granatum fruit ferment extract, sodium hydroxide, pentylene glycol, allantoin, ceteth-20, dipotassium glycyrrhizate, disodium EDTA, PEG-60 almond glycerides, butylene glycol, glycerin, maltodextrin, aloe barbadensis leaf juice, dextrin, rosa damascena flower extract, leuconostoc/radish root ferment filtrate, lecithin, syringa vulgaris (lilac) extract, bisabolol, punica granatum fruit extract, phenoxyethanol, rosa centifolia flower extract, salvia hispanica (chia) seed oil, chlorphenesin, red 4 (CI 14700), ceramide NP, beta-sitosterol, perilla ocymoides leaf extract, oenothera biennis (evening primrose) oil, perilla ocymoides seed oil, tocopherol, glycine soja (soybean) oil, potassium sorbate, sodium benzoate, BHT, helianthus annuus (sunflower) seed oil.